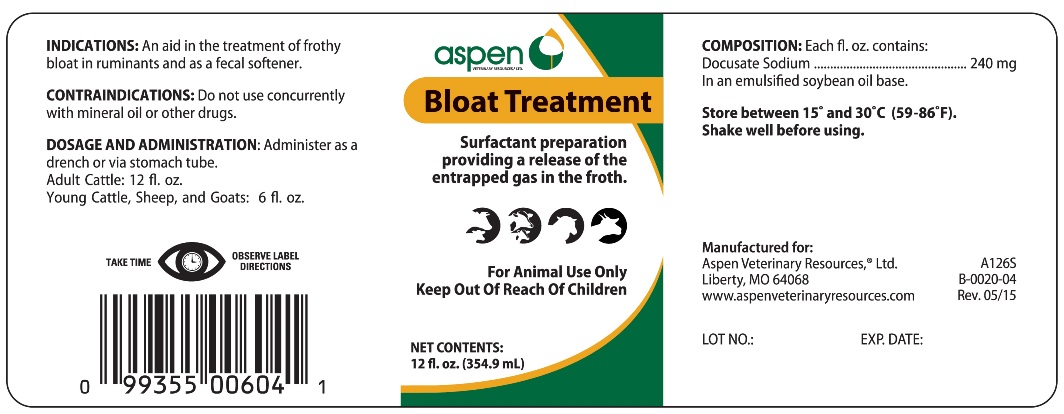 DRUG LABEL: BLOAT TREATMENT
NDC: 46066-200 | Form: EMULSION
Manufacturer: Aspen Veterinary Resources, Ltd
Category: animal | Type: OTC ANIMAL DRUG LABEL
Date: 20220103

ACTIVE INGREDIENTS: DOCUSATE SODIUM 240 mg/29.57 mL

BLOAT TREATMENT

INDICATIONS AND USAGE

Surfactant preparation providing a release of the entrapped gas in the froth.

For Animal Use Only

Keep Out of Reach of Children

INDICATIONS

An aid in the treatment of frothy bloat in ruminants and as a fecal softener.

CONTRAINDICATION

Do not use concurrently with mineral oil or other drugs.

DOSAGE AND ADMINISTRATION

Administer as a drench or via stomach tube.

Adult Cattle: 12 fl.oz.

Young Cattle, Sheep and Goats: 6 fl.oz.

COMPOSITION

Each fl.oz. contains:

Docusate Sodium ................................... 240 mg

In an emulsified soybean oil base

STORAGE AND HANDLING

Store between 15° and 30°C (59° - 86°F)

Shake well before using.